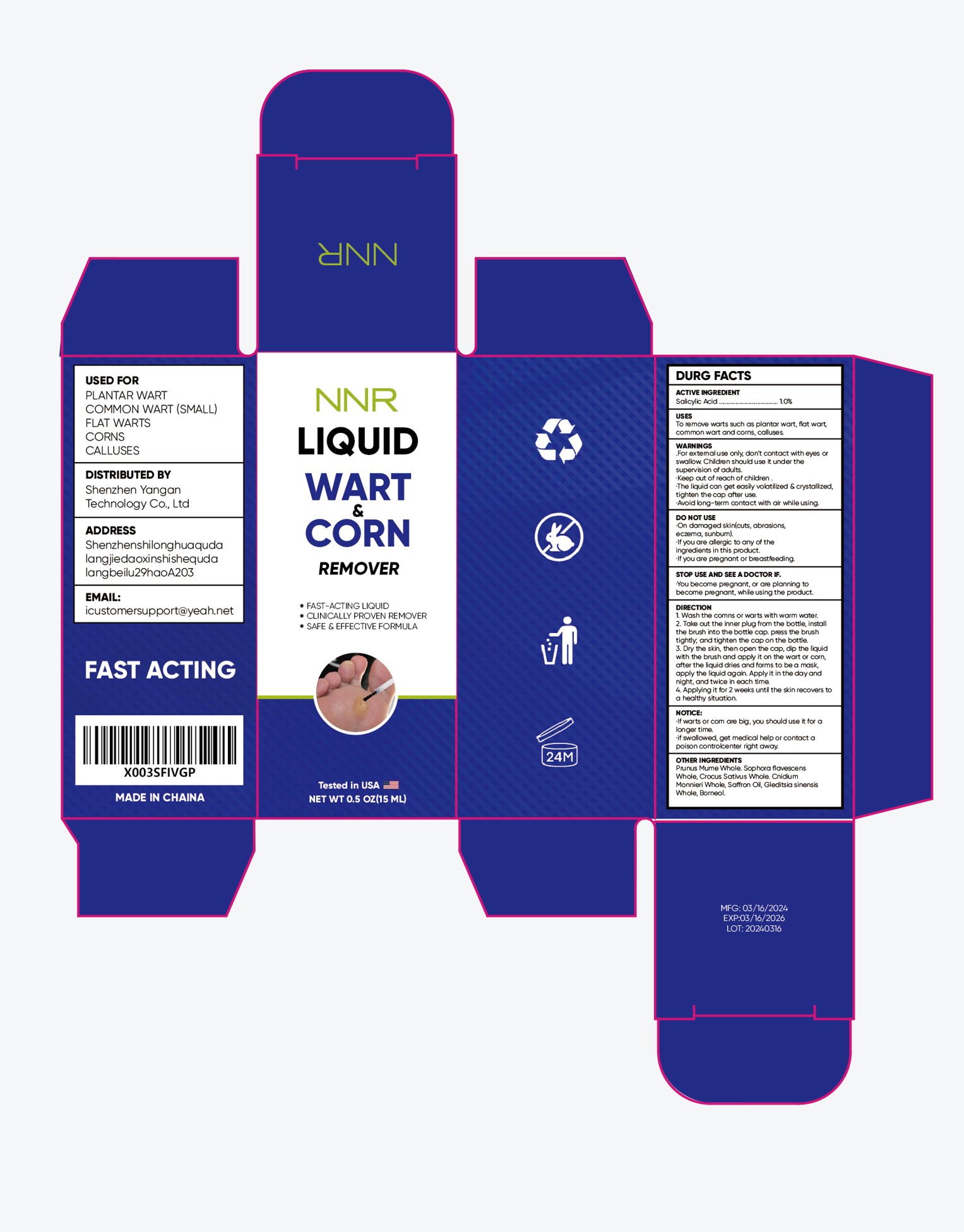 DRUG LABEL: Nnr Liquid Wart  Corn Remover
NDC: 84023-801 | Form: LIQUID
Manufacturer: Shenzhen Yangan Technology Co., Ltd.
Category: otc | Type: HUMAN OTC DRUG LABEL
Date: 20240402

ACTIVE INGREDIENTS: SALICYLIC ACID 1 g/100 mL
INACTIVE INGREDIENTS: BORNEOL; PRUNUS MUME FLOWER; SOPHORA FLAVESCENS ROOT; CNIDIUM MONNIERI WHOLE; SAFFRON OIL; CROCUS SATIVUS WHOLE; GLEDITSIA SINENSIS WHOLE

NNR LIQUID WART & CORN REMOVER

NNR LIQUID WART & CORN REMOVER

ACTIVE INGREDIENT

Salicylic acid 1%

PURPOSE

To remove warts such as plantar wart, flat wart,common wart and corns, calluses

INDICATIONS AND USAGE

To remove warts such as plantar wart, flat wart,common wart and corns, calluses

WARNINGS

For external use only don't contact with eyes or swallow Children should use it under the supervision of adults.
Keep out of reach of children.
The liquid can get easily volatilized & crystallized,tighten the cap after use.
Avoid long-term contact with air while using.

DO NOT USE

On damaged skin(cuts, abrasions eczema, sunbum).
If you are allergic to any of the ingredients in this product.
If you are pregnant or breastfeeding.

WHEN USING

For external use only don't contact with eyes or swallow Children should use it under the supervision of adults.
Keep out of reach of children.
The liquid can get easily volatilized & crystallized,tighten the cap after use.
Avoid long-term contact with air while using.

STOP USE

You become pregnant, or are planning to become pregnant, while using the product.

Keep out of reach of children

DOSAGE AND ADMINISTRATION

1. Wash the comns or warts with warm water.
2. Take out the inner plug from the bottle, install the brush into the bottle cap. press the brush tightly: and tighten the cap on the bottle.
3. Dry the skin, then open the cap, dip the liquid with the brush and apply it on the wart or corn, after the liquid dries and forms to be a mask ,apply the liquid again. Apply it in the day and night, and twice in each time.
4. Applying it for 2 weeks unti the skin recovers to a healthy situation.

STORAGE AND HANDLING

Store in a dark and cool place.

INACTIVE INGREDIENT

Prunus Mume(sieb)
Sophora flavescens
Crocus Sativus L
Cnidium Monnieri(L) Cuss
Kochia scoparia(L)Schrad
cortex dictamni
Gleditsia sinensis Lam.
Borneol